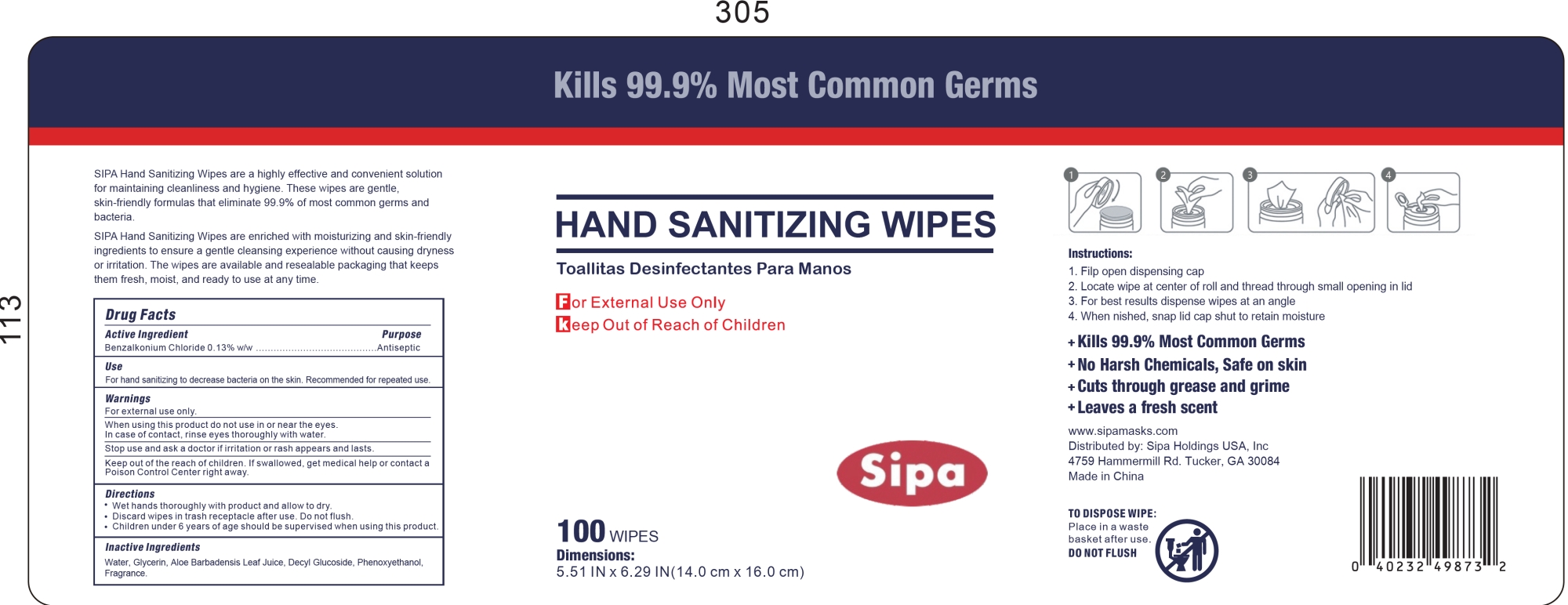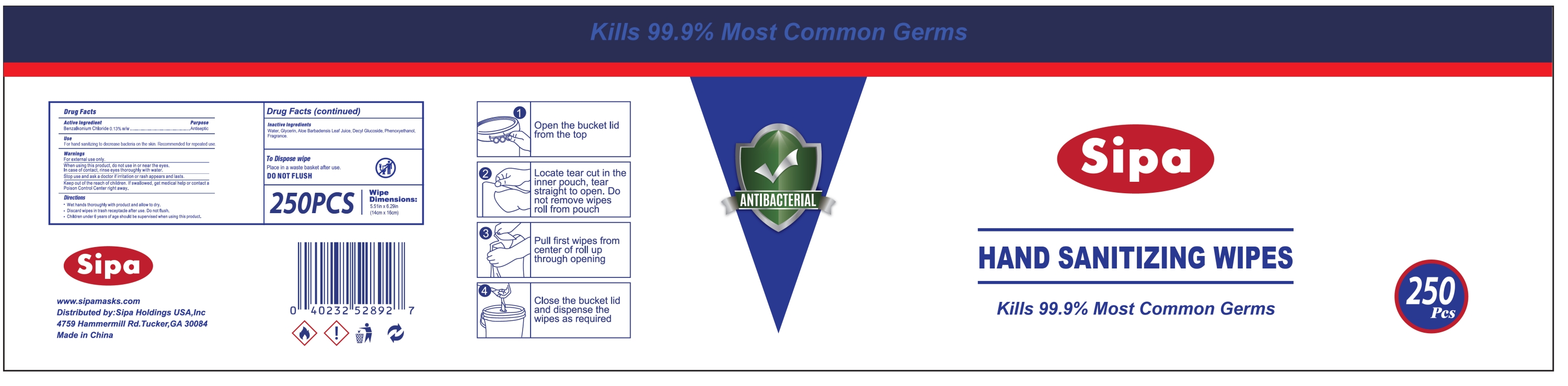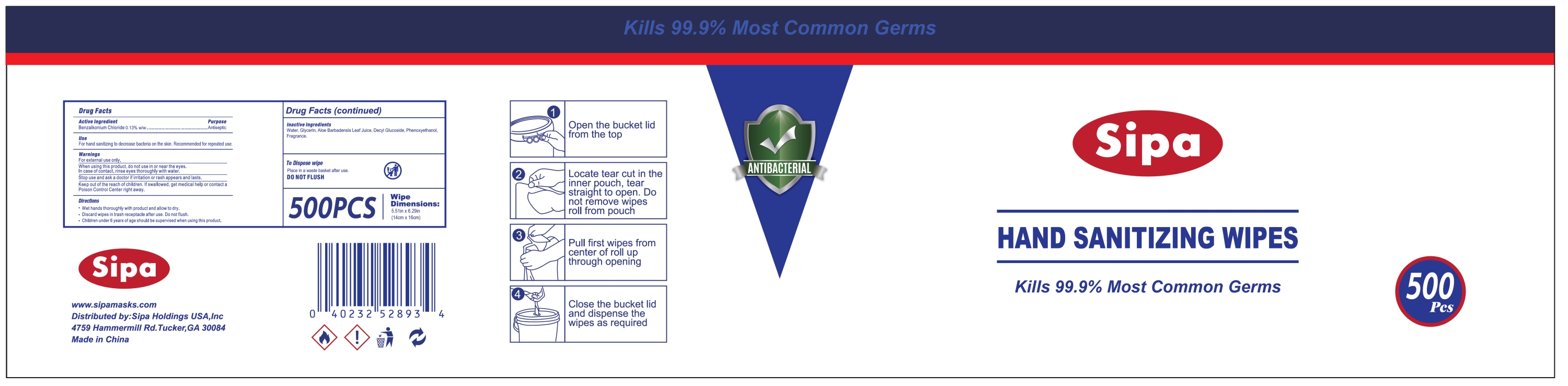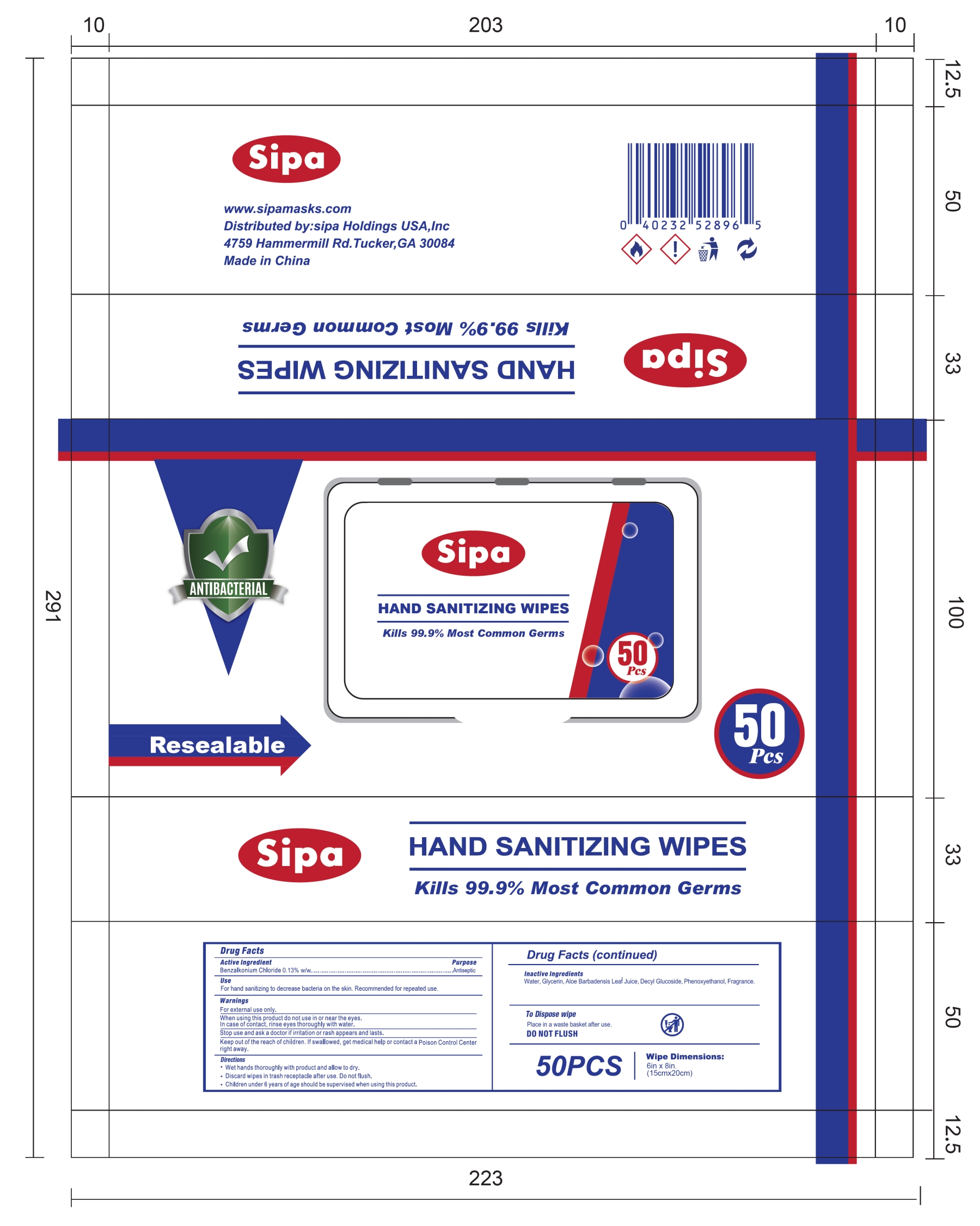 DRUG LABEL: Sipa HAND SANITIZING WIPES
NDC: 85137-001 | Form: CLOTH
Manufacturer: Sipa Holdings USA, Inc.
Category: otc | Type: HUMAN OTC DRUG LABEL
Date: 20251223

ACTIVE INGREDIENTS: BENZALKONIUM CHLORIDE 0.13 g/100 g
INACTIVE INGREDIENTS: DECYL GLUCOSIDE; WATER; ALOE BARBADENSIS LEAF; PHENOXYETHANOL; GLYCERIN

85137-001 Sipa HAND SANITIZING WIPES

Active Ingredient

Benzalkonium Chloride 0.13% w/w

Purpose

Antiseptic

Use

For hands sanitizing to decrease bacteria on the skin. Recommended for repeated use.

Warnings

For external use only.

When using this product do not use in or near the eyes.

In case of contact, rinse eyes thoroughly with water.

Stop use and ask a doctor if irritation or rash appears and lasts.

KEEP OUT OF REACH OF CHILDREN

Keep out of the reach of children. If swallowed, get medical help or contact a Poison Control Center right away.

Directions

· Wet hands thoroughly with product and allow to dry.

· Discard wipes in trash receptacle after use. Do not flush.

· Children under 6 years of age should be supervised when using this product.

Inactive Ingredients

Water, Glycerin, Aloe Barbadensis Leaf Juice, Decyl Glucoside, Phenoxyethanol, Fragrance.

PACKAGE LABEL

50PCS
NDC: 85137-001-01

PACKAGE LABEL

100 WIPES
NDC: 85137-001-02

PACKAGE LABEL

250PCS
NDC: 85137-001-03

PACKAGE LABEL

500PCS
NDC: 85137-001-04